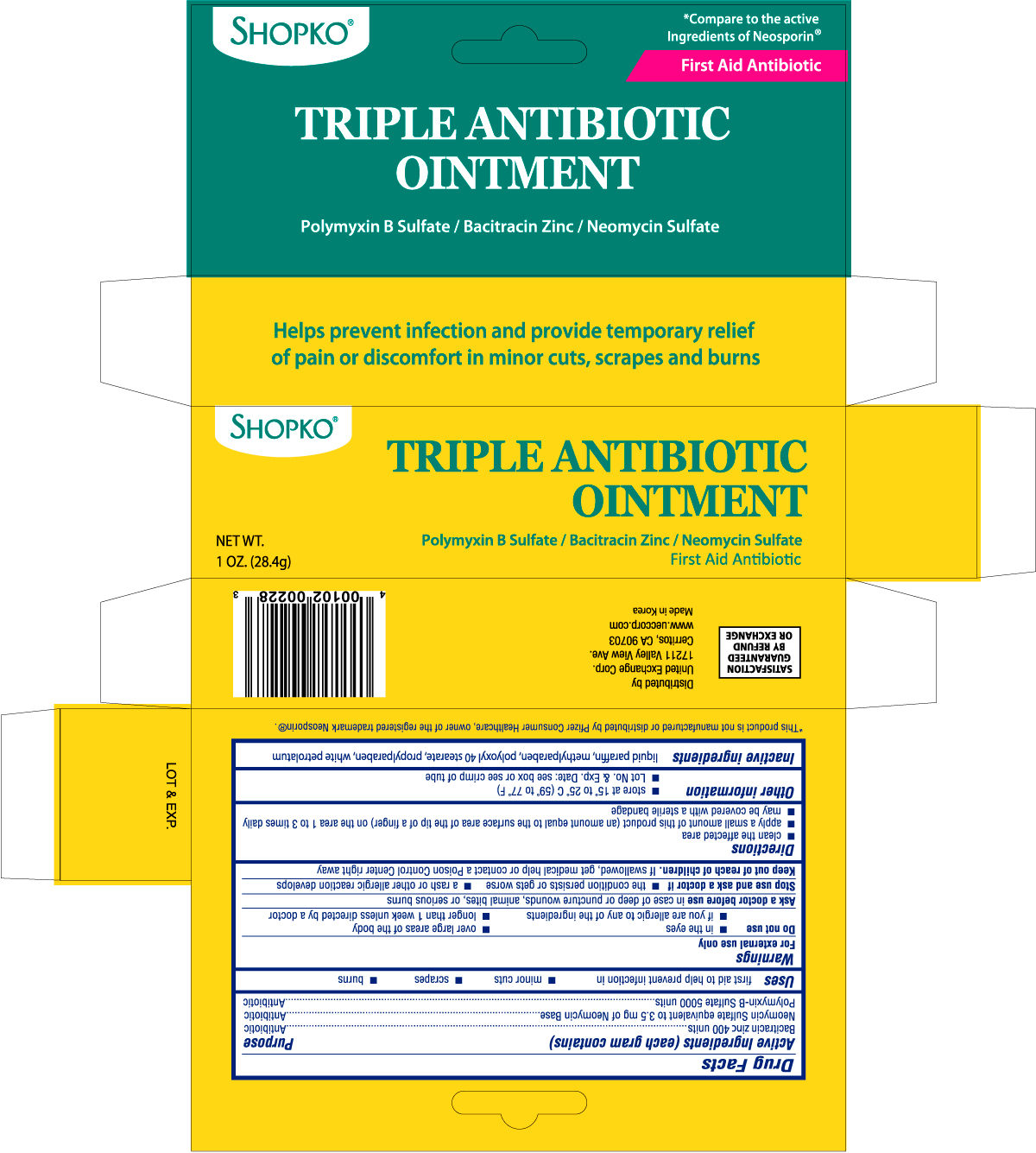 DRUG LABEL: SHOPKO TRIPLE ANTIBIOTIC
NDC: 68169-0022 | Form: OINTMENT
Manufacturer: TAI GUK PHARM. CO., LTD.
Category: otc | Type: HUMAN OTC DRUG LABEL
Date: 20101220

ACTIVE INGREDIENTS: BACITRACIN ZINC 400 [iU]/1 g; NEOMYCIN SULFATE  3.5 mg/1 g; POLYMYXIN B SULFATE 5000 [iU]/1 g
INACTIVE INGREDIENTS: MINERAL OIL; METHYLPARABEN; POLYOXYL 40 STEARATE; PROPYLPARABEN; PETROLATUM

Drug Facts

Active Ingredients (each gram contains) Purpose

Bacitracin zinc 400 units ........................................................................................Antibiotic

Neomycin Sulfate equivalent to 3.5mg of Neomycin Base ........................................Antibiotic

Polymyxin-B Sulfate 5000 units ..............................................................................Antibiotic

Uses

first aid to help prevent infection in

- minor cuts
- scrapes
- burns

Warnings

For external use only

Do not use

- in the eyes
- if you are allergic to any of the ingredients
- over large areas of the body
- longer than 1 week unless directed by a doctor

Ask a doctor before use in case of deep or puncture wounds, animal bites, or serious burns

Stop use and ask a doctor if

- the condition persists or gets worse
- a rash or other allergic reaction develops

Keep out of reach of children. If swallowed, get medical help or contact a Poison Control Center right away

Directions

- clean the affected area
- apply a small amount of this product (an amount equal to the surface area of the tip of a finger) on the area 1 to 3 times daily
- may be covered with a sterile bandage

Other information

- store at 15o to 25oC (59o to 77oF)
- Lot No. and Exp. Date: see box or see crimp of tube

Inactive ingredients

liquid paraffin, methylparaben, polyoxyl 40 stearate, propylparaben, white petrolatum

DOSAGE AND ADMINISTRATION

Distributed by

United Exchange Corp.

17211 Valley View Ave.

Cerritos, CA 90703

www.ueccorp.com

Made in Korea

PACKAGE LABEL

Enter section text here